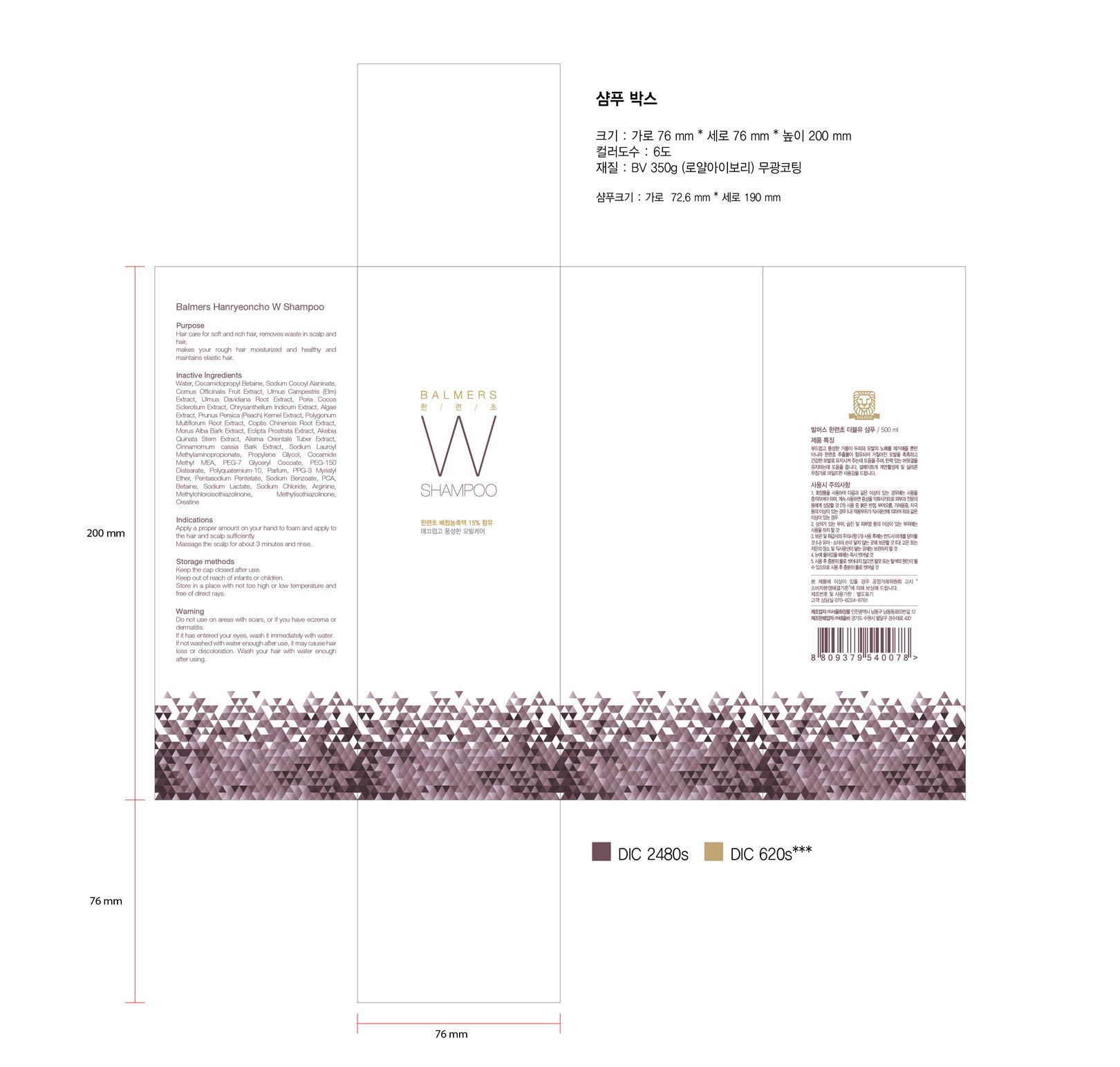 DRUG LABEL: Balmers Hanryeoncho W
NDC: 69927-002 | Form: SHAMPOO
Manufacturer: Tae Eul Bi Co., Ltd.
Category: otc | Type: HUMAN OTC DRUG LABEL
Date: 20150720

ACTIVE INGREDIENTS: COCAMIDOPROPYL BETAINE 24 g/100 mL
INACTIVE INGREDIENTS: WATER; SODIUM CHLORIDE

Drug Facts

ACTIVE INGREDIENT

cocamidopropyl betaine

INACTIVE INGREDIENT

water, sodium cocoyl alaninate, cornus officinalis fruit ext, creatine, etc.

PURPOSE

hair grower and hair loss prevention

keep out of reach of the children

INDICATIONS AND USAGE

apply proper amount on your hand to foam and apply to the hair and scalp sufficientlymassage the scalp for about 3 minutes and rinse

WARNINGS

1. Do not use in the following cases(Eczema and scalp wounds)
2.Side Effects
1)Due to the use of this druf if rash, irritation, itching and symptopms of hypersnesitivity occur dicontinue use and consult your phamacisr or doctor
3.General Precautions
1)If in contact with the eyes, wash out thoroughty with water If the symptoms are servere, seek medical advice immediately
2)This product is for exeternal use only. Do not use for internal use
4.Storage and handling precautions
1)If possible, avoid direct sunlight and store in cool and area of low humidity
2)In order to maintain the quality of the product and avoid misuse
3)Avoid placing the product near fire and store out in reach of children

DOSAGE AND ADMINISTRATION

for external use only